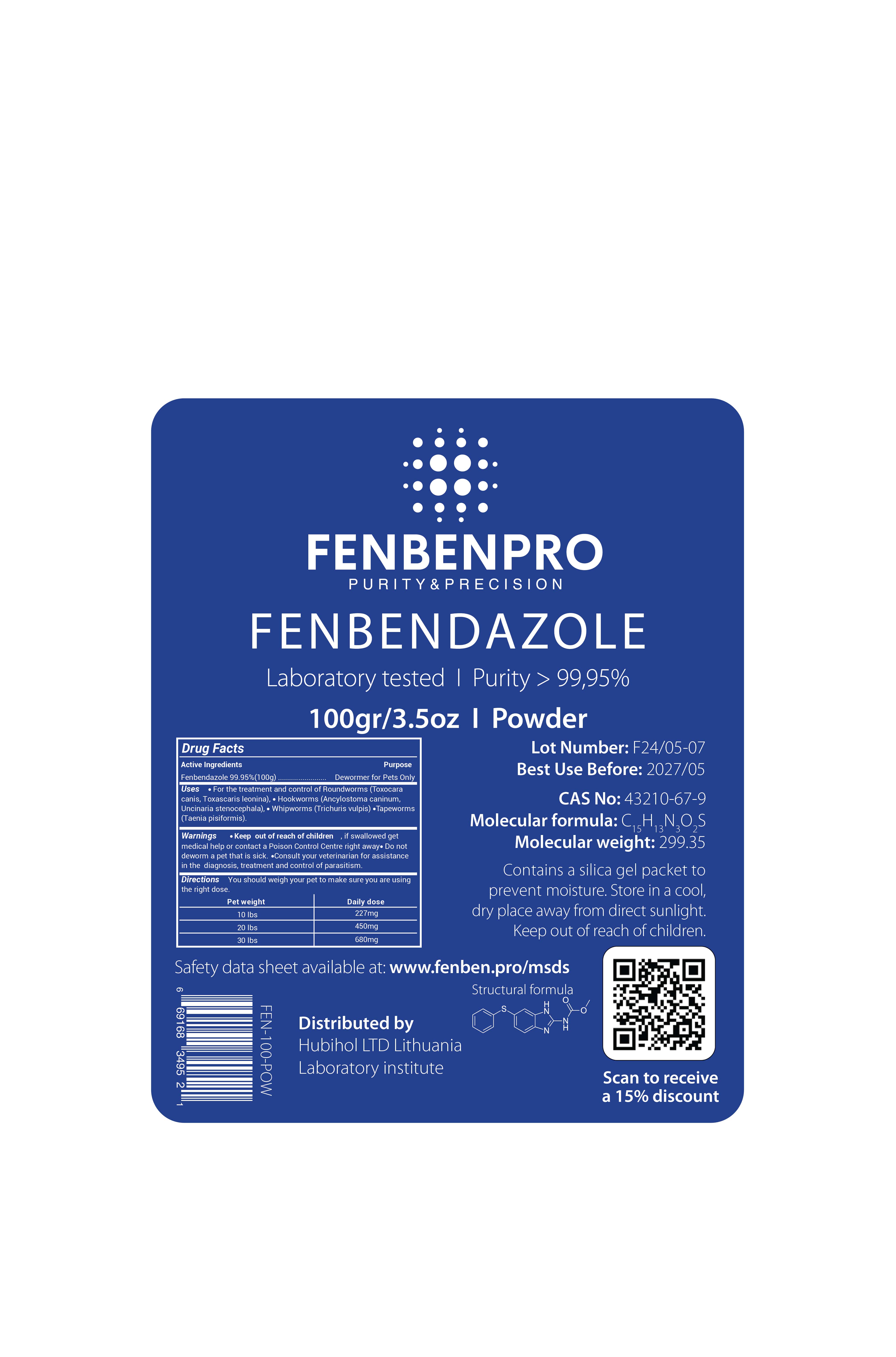 DRUG LABEL: FENBENPRO
NDC: 86217-0003 | Form: POWDER
Manufacturer: HUBIHOL, UAB
Category: animal | Type: OTC ANIMAL DRUG LABEL
Date: 20250128

ACTIVE INGREDIENTS: FENBENDAZOLE 100 g/100 g

FENBENPRO

Active Ingredients

Fenbendazole 99.95%

Package Labeling

Drug Facts
Active Ingredients
FENBENPRO
PURITY & PRECISION
FENBENDAZOLE
Laboratory tested | Purity > 99,95%
Fenbendazole 99.95% (100g)
100gr/3.5oz | Powder
Purpose Dewormer for Pets Only Uses • For the treatment and control of Roundworms (Toxocara canis, Toxascaris leonina), • Hookworms (Ancylostoma caninum, Uncinaria stenocephala), • Whipworms (Trichuris vulpis) •Tapeworms (Taenia pisiformis).
Warnings
Keep out of reach of children if swallowed get medical help or contact a Poison Control Centre right away. Do not deworm a pet that is sick. Consult your veterinarian for assistance in the diagnosis, treatment and control of parasitism.
Directions You should weigh your pet to make sure you are using the right dose.
Pet weight
10 lbs
20 lbs
30 lbs
Daily dose
227mg
450mg
680mg
Lot Number: F24/05-07 Best Use Before: 2027/05
CAS No: 43210-67-9
Molecular formula: C1H12N2O,S
15 13 3
2
Molecular weight: 299.35 Contains a silica gel packet to prevent moisture. Store in a cool, dry place away from direct sunlight. Keep out of reach of children.
Safety data sheet available at: www.fenben.pro/msds
9
69168 3495 2
1
FEN-100-POW
Distributed by
Hubihol LTD Lithuania Laboratory institute
Structural formula
Scan to receive a 15% discount